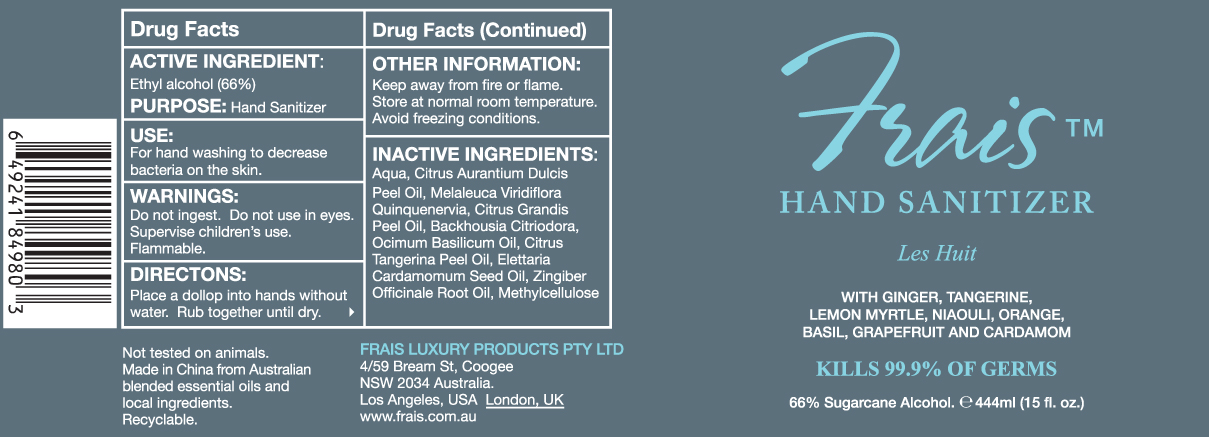 DRUG LABEL: Frais Hand Sanitizer
NDC: 42587-001 | Form: GEL
Manufacturer: Frais Luxury Products
Category: otc | Type: HUMAN OTC DRUG LABEL
Date: 20091202

ACTIVE INGREDIENTS: ALCOHOL 66 g/100 g
INACTIVE INGREDIENTS: METHYLCELLULOSE (100 CPS) 1 g/100 g; WATER 32 g/100 g; VACCINIUM MYRTILLUS LEAF; ORANGE; GRAPEFRUIT; TANGERINE; CARDAMOM; MELALEUCA QUINQUENERVIA POLLEN; BASIL; GINGER

Frais Hand Sanitizer

ACTIVE INGREDIENT

Ethyl alcohol (66%)

USE

For hand washing to decrease bacteria on the skin.

WARNINGS

Do not ingest. Do not use in eyes. Supervise children’s use. Flammable.

DIRECTIONS

Place a dollop into hands without water. Rub together until dry.

OTHER INFORMATION

Keep away from fire or flame. Store at normal room temperature. Avoid freezing conditions.

INACTIVE INGREDIENTS

Aqua, Citrus Aurantium Dulcis Peel Oil, Melaleuca Quinquenervia Oil, Citrus Grandis Peel Oil, Backhousia Citriodora Leaf Oil, Ocimum Basilicum Oil, Citrus Tangerina Peel Oil, Elettaria Cardamomum Seed Oil, Zingiber Officinale Root Oil, Methylcellulose

PATIENT COUNSELING INFORMATION

Not tested on animals. Made in China from Australian blended essential oils and local ingredients. Recyclable.

HOW SUPPLIED

FRAIS LUXURY PRODUCTS PTY LTD
4/59 Bream St, Coogee NSW 2034 Australia.
Los Angeles, USA London, UK
www.frais.com.au

PACKAGE LABEL

Frais™

HAND SANITIZER
Les Huit
WITH GINGER, TANGERINE,
LEMON MYRTLE, NIAOULI, ORANGE,
BASIL, GRAPEFRUIT AND CARDAMOM
KILLS 99.9% OF GERMS
66% Sugarcane Alcohol. ℮ 444ml (15fl. oz.)